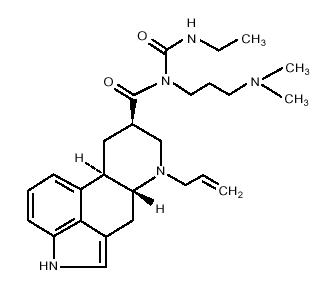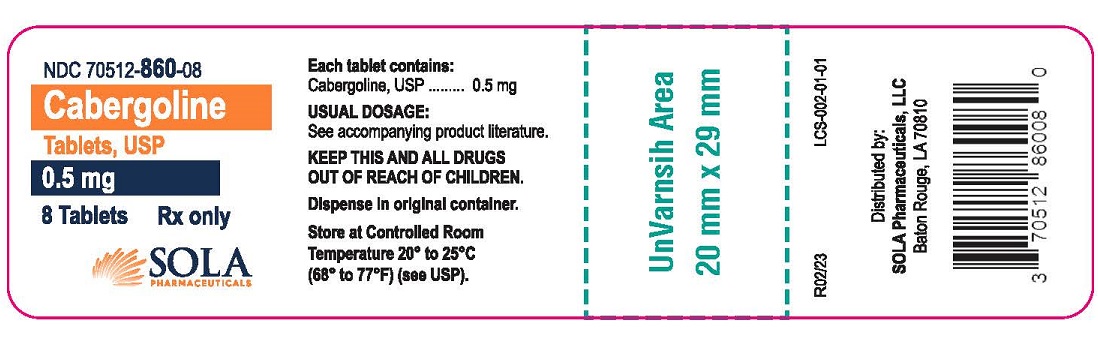 DRUG LABEL: Cabergoline
NDC: 70512-860 | Form: TABLET
Manufacturer: SOLA Pharmaceuticals, LLC
Category: prescription | Type: HUMAN PRESCRIPTION DRUG LABEL
Date: 20251208

ACTIVE INGREDIENTS: CABERGOLINE 0.5 mg/1 1
INACTIVE INGREDIENTS: CITRIC ACID MONOHYDRATE; CROSCARMELLOSE SODIUM; MAGNESIUM STEARATE; MICROCRYSTALLINE CELLULOSE

CABERGOLINE TABLETS
Rx only

DESCRIPTION

Cabergoline Tablets, USP contain cabergoline USP, a dopamine receptor agonist. The chemical name for cabergoline USP is 1-[(6-allylergolin-8ß-yl)-carbonyl]-1-[3-(dimethylamino)propyl]-3-ethylurea. Its molecular formula is C26H37N5O2, and its molecular weight is 451.62. The structural formula is as follows:

Cabergoline USP is a white powder soluble in ethyl alcohol, chloroform, and N, N-dimethylformamide (DMF); slightly soluble in 0.1N hydrochloric acid; very slightly soluble in n-hexane; and insoluble in water.

Each tablet, for oral administration, contains 0.5 mg of cabergoline USP. Inactive ingredients consist of citric acid, croscarmellose sodium, magnesium stearate and microcrystalline cellulose.

CLINICAL PHARMACOLOGY

Mechanism of Action:

The secretion of prolactin by the anterior pituitary is mainly under hypothalamic inhibitory control, likely exerted through release of dopamine by tuberoinfundibular neurons. Cabergoline is a long-acting dopamine receptor agonist with a high affinity for D2 receptors. Results of in vitro studies demonstrate that cabergoline exerts a direct inhibitory effect on the secretion of prolactin by rat pituitary lactotrophs. Cabergoline decreased serum prolactin levels in reserpinized rats. Receptor-binding studies indicate that cabergoline has low affinity for dopamine D1, a1- and a2-adrenergic, and 5-HT1- and 5-HT2-serotonin receptors.

Clinical Studies:

The prolactin-lowering efficacy of cabergoline was demonstrated in hyperprolactinemic women in two randomized, double-blind, comparative studies, one with placebo and the other with bromocriptine. In the placebo-controlled study (placebo n=20; cabergoline n=168), cabergoline produced a dose-related decrease in serum prolactin levels with prolactin normalized after 4 weeks of treatment in 29%, 76%, 74% and 95% of the patients receiving 0.125, 0.5, 0.75, and 1 mg twice weekly, respectively.

In the 8-week, double-blind period of the comparative trial with bromocriptine (cabergoline n=223; bromocriptine n=236 in the intent-to-treat analysis), prolactin was normalized in 77% of the patients treated with cabergoline at 0.5 mg twice weekly compared with 59% of those treated with bromocriptine at 2.5 mg twice daily. Restoration of menses occurred in 77% of the women treated with cabergoline, compared with 70% of those treated with bromocriptine. Among patients with galactorrhea, this symptom disappeared in 73% of those treated with cabergoline compared with 56% of those treated with bromocriptine.

Pharmacokinetics

Absorption:

Following single oral doses of 0.5 mg to 1.5 mg given to 12 healthy adult volunteers, mean peak plasma levels of 30 to 70 picograms (pg)/mL of cabergoline were observed within 2 to 3 hours. Over the 0.5 to 7 mg dose range, cabergoline plasma levels appeared to be dose-proportional in 12 healthy adult volunteers and nine adult parkinsonian patients. A repeat-dose study in 12 healthy volunteers suggests that steady-state levels following a once-weekly dosing schedule are expected to be twofold to threefold higher than after a single dose. The absolute bioavailability of cabergoline is unknown. A significant fraction of the administered dose undergoes a first-pass effect. The elimination half-life of cabergoline estimated from urinary data of 12 healthy subjects ranged between 63 to 69 hours. The prolonged prolactin-lowering effect of cabergoline may be related to its slow elimination and long half-life.

Distribution:

In animals, based on total radioactivity, cabergoline (and/or its metabolites) has shown extensive tissue distribution. Radioactivity in the pituitary exceeded that in plasma by >100-fold and was eliminated with a half-life of approximately 60 hours. This finding is consistent with the long-lasting prolactin-lowering effect of the drug. Whole body autoradiography studies in pregnant rats showed no fetal uptake but high levels in the uterine wall. Significant radioactivity (parent plus metabolites) detected in the milk of lactating rats suggests a potential for exposure to nursing infants. The drug is extensively distributed throughout the body. Cabergoline is moderately bound (40% to 42%) to human plasma proteins in a concentration-independent manner. Concomitant dosing of highly protein-bound drugs is unlikely to affect its disposition.

Metabolism:

In both animals and humans, cabergoline is extensively metabolized, predominately via hydrolysis of the acylurea bond or the urea moiety. Cytochrome P-450 mediated metabolism appears to be minimal. Cabergoline does not cause enzyme induction and/or inhibition in the rat. Hydrolysis of the acylurea or urea moiety abolishes the prolactin-lowering effect of cabergoline, and major metabolites identified thus far do not contribute to the therapeutic effect.

Excretion:

After oral dosing of radioactive cabergoline to five healthy volunteers, approximately 22% and 60% of the dose was excreted within 20 days in the urine and feces, respectively. Less than 4% of the dose was excreted unchanged in the urine. Nonrenal and renal clearances for cabergoline are about 3.2 L/min and 0.08 L/min, respectively. Urinary excretion in hyperprolactinemic patients was similar.

Special Populations

Renal Insufficiency:

The pharmacokinetics of cabergoline were not altered in 12 patients with moderate-to severe renal insufficiency as assessed by creatinine clearance.

Hepatic Insufficiency:

In 12 patients with mild-to-moderate hepatic dysfunction (Child-Pugh score £10), no effect on mean cabergoline Cmax or area under the plasma concentration curve (AUC) was observed. However, patients with severe insufficiency (Child-Pugh score >10) show a substantial increase in the mean cabergoline Cmax and AUC, and thus necessitate caution.

Elderly:

Effect of age on the pharmacokinetics of cabergoline has not been studied.

Food-Drug Interaction:

In 12 healthy adult volunteers, food did not alter cabergoline kinetics.

Pharmacodynamics

Dose response with inhibition of plasma prolactin, onset of maximal effect, and duration of effect has been documented following single cabergoline doses to healthy volunteers (0.05 to 1.5 mg) and hyperprolactinemic patients (0.3 to 1 mg). In volunteers, prolactin inhibition was evident at doses >0.2 mg, while doses ≥ 0.5 mg caused maximal suppression in most subjects. Higher doses produce prolactin suppression in a greater proportion of subjects and with an earlier onset and longer duration of action. In 12 healthy volunteers, 0.5, 1 and 1.5 mg doses resulted in complete prolactin inhibition, with a maximum effect within 3 hours in 92% to 100% of subjects after the 1 and 1.5 mg doses compared with 50% of subjects after the 0.5 mg dose.

In hyperprolactinemic patients (n=51), the maximal prolactin decrease after a 0.6 mg single dose of cabergoline was comparable to 2.5 mg bromocriptine; however, the duration of effect was markedly longer (14 days vs. 24 hours). The time to maximal effect was shorter for bromocriptine than cabergoline (6 hours vs. 48 hours).

In 72 healthy volunteers, single or multiple doses (up to 2 mg) of cabergoline resulted in selective inhibition of prolactin with no apparent effect on other anterior pituitary hormones (GH, FSH, LH, ACTH, and TSH) or cortisol.

INDICATIONS AND USAGE

Cabergoline Tablets, USP are indicated for the treatment of hyperprolactinemic disorders, either idiopathic or due to pituitary adenomas.

CONTRAINDICATIONS

Cabergoline Tablets, USP are contraindicated in patients with

- Uncontrolled hypertension or known hypersensitivity to ergot derivatives.
- History of cardiac valvular disorders, as suggested by anatomical evidence of valvulopathy of any valve, determined by pre-treatment evaluation including echocardiographic demonstration of valve leaflet thickening, valve restriction, or mixed valve restriction-stenosis (See WARNINGS).
- History of pulmonary, pericardial, or retroperitoneal fibrotic disorders (See WARNINGS).

WARNINGS

1. Pregnancy:

Dopamine agonists in general should not be used in patients with pregnancy-induced hypertension, for example, preeclampsia, eclampsia, and postpartum hypertension, unless the potential benefit is judged to outweigh the possible risk.

2. Fibrotic Complications:

a. Cardiac Valvulopathy:

All patients should undergo a cardiovascular evaluation, including echocardiogram to assess the potential presence of valvular disease. If valvular disease is detected, the patient should not be treated with Cabergoline (See CONTRAINDICATIONS) . Post-marketing cases of cardiac valvulopathy have been reported in patients receiving Cabergoline. These cases have generally occurred during administration of high doses of Cabergoline (>2mg/day) used for the treatment of Parkinson’s disease. Cases of cardiac valvulopathy have also been reported in patients receiving lower doses for the treatment of hyperprolactinemic disorders.

A multi-country, retrospective cohort study using general practice records and record linkage systems in the UK, Italy and the Netherlands was conducted to assess the association between new use of dopamine agonists including cabergoline (n=27,812) for Parkinson’s disease and hyperprolactinemia and cardiac valvular regurgitation (CVR), other fibroses, and other cardiopulmonary events over a maximum of 12 years of follow up. In this study, the use of cabergoline among persons with Parkinson’s disease was associated with an increased risk of CVR when compared to non-ergot-derived dopamine agonists (Das) and levodopa [Incidence Rate (IR) per 10,000 person years of 68.1 (95% confidence interval (CI): 37.2 to 115.3) for cabergoline vs. 10.0 (95% CI: 5.2 to 19.4) for non-ergot Das and 11.3 (95% CI: 7.2 to 17.0) for levodopa]. In the study analysis confined to persons with dopamine agonist-treated hyperprolactinemia (n=8,386), when compared to non-use (n=15,147), persons exposed to cabergoline did not have an elevated risk of CVR. The findings with respect to the risk of CVR associated with cabergoline treatment for persons with Parkinson’s disease (increased risk) and those with hyperprolactinemia (no increased risk) are consistent with the findings in other published studies.

Physicians should use the lowest effective dose of Cabergoline for the treatment of hyperprolactinemic disorders and should periodically reassess the need for continuing therapy with Cabergoline. Following treatment initiation, clinical and diagnostic monitoring (for example, chest x-ray, CT scan and cardiac echocardiogram) should be conducted to assess the risk of cardiac valvulopathy. The recommended frequency of routine echocardiographic monitoring is every 6 to 12 months or as clinically indicated with the presence of signs and symptoms such as edema, new cardiac murmer, dyspnea or congestive heart failure.

Cabergoline should be discontinued if an echocardiogram reveals new valvular regurgitation, valvular restriction or valve leaflet thickening.

Cabergoline should be used with caution in patients exposed to other medications associated with valvulopathy.

b. Extracardiac Fibrotic Reactions:

Post-marketing cases of pleural, pericardial and retroperitoneal fibrosis have been following administration of Cabergoline. Some reports were in patients previously treated with other ergotinic dopamine agonists. Cabergoline should not be used in patients with a history of cardiac or extracardiac fibrotic disorders.

Fibrotic disorders can have an insidious onset and patients should be monitored for manifestations of progressive fibrosis. Therefore, during treatment, attention should be paid to the signs and symptoms of:

- Pleuro-pulmonary disease such as dyspnea, shortness of breath, persistent cough or chest pain.
- Renal insufficiency or ureteral/abdominal vascular obstruction that may occur with pain in the loin/flank and lower limb edema as well as any possible abdominal masses or tenderness that may indicate retroperitoneal fibrosis.
- Cardiac failure: Cases of valvular and pericardial fibrosis have ofter manifested as cardiac failure. Therefore, valvular fibrosis (and constrictive pericarditis) should be excluded if such symptoms occur.

Clinical and diagnostic monitoring such as erythrocyte sedimentation rate, chest x-ray, serum creatinine measurements, and other investigations should be considered at baseline and as necessary while patients are treated with Cabergoline.

Following diagnosis of pleural effusion or pulmonary fibrosis, the discontinuance of Cabergoline was reported to result in improvement of signs and symptoms.

PRECAUTIONS

General:

Initial doses higher than 1.0 mg may produce orthostatic hypotension. Care should be exercised when administering cabergoline with other medications known to lower blood pressure.

Postpartum Lactation Inhibition or Suppression:

Cabergoline is not indicated for the inhibition or suppression of physiologic lactation. Use of bromocriptine, another dopamine agonist for this purpose, has been associated with cases of hypertension, stroke, and seizures.

Hepatic Impairment:

Since cabergoline is extensively metabolized by the liver, caution should be used, and careful monitoring exercised, when administering cabergoline to patients with hepatic impairment.

Psychiatric:

Impulse control/compulsive behaviors, including pathological gambling, increased libido, and hypersexuality, have been reported in patients treated with dopamine agonists including cabergoline. This has been generally reversible upon reduction of the dose or treatment discontinuation (see Post-marketing Surveillance data). Prescribers should consider dose reduction or stopping the medication if a patient develops such urges while taking cabergoline.

Information for Patients:

Patients should be instructed to notify their physician if they suspect they are pregnant, become pregnant, or intend to become pregnant during therapy. A pregnancy test should be done if there is any suspicion of pregnancy and continuation of treatment should be discussed with their physician.

Patients should notify their physician if they develop shortness of breath, persistent cough, difficulty with breathing when lying down, or swelling in their extremities.

Patients should be alerted to the possibility that patients may experience intense urges to spend money uncontrollably, intense urges to gamble, increased sexual urges, and other intense urges and the inability to control these urges while taking cabergoline. Advise patients to inform their healthcare provider if they develop new or increased uncontrolled spending, gambling urges, sexual urges, or other urges while being treated with cabergoline (see PRECAUTIONS).

Drug Interactions:

Cabergoline should not be administered concurrently with D2-antagonists, such as phenothiazines, butyrophenones, thioxanthenes, or metoclopramide.

Carcinogenesis, Mutagenesis, Impairment of Fertility:

Carcinogenicity studies were conducted in mice and rats with cabergoline given by gavage at doses up to 0.98 mg/kg/day and 0.32 mg/kg/day, respectively. These doses are 7 times and 4 times the maximum recommended human dose calculated on a body surface area basis using total mg/m^2/week in rodents and mg/m^2/week for a 50 kg human.

There was a slight increase in the incidence of cervical and uterine leiomyomas and uterine leiomyosarcomas in mice. In rats, there was a slight increase in malignant tumors of the cervix and uterus and interstitial cell adenomas. The occurrence of tumors in female rodents may be related to the prolonged suppression of prolactin secretion because prolactin is needed in rodents for the maintenance of the corpus luteum. In the absence of prolactin, the estrogen/progesterone ratio is increased, thereby increasing the risk for uterine tumors. In male rodents, the decrease in serum prolactin levels was associated with an increase in serum luteinizing hormone, which is thought to be a compensatory effect to maintain testicular steroid synthesis. Since these hormonal mechanisms are thought to be species-specific, the relevance of these tumors to humans is not known.

The mutagenic potential of cabergoline was evaluated and found to be negative in a battery of in vitro tests. These tests included the bacterial mutation (Ames) test with Salmonella typhimurium, the gene mutation assay with Schizosaccharomyces pombe P1 and V79 Chinese hamster cells, DNA damage and repair in Saccharomyces cerevisiae D4, and chromosomal aberrations in human lymphocytes. Cabergoline was also negative in the bone marrow micronucleus test in the mouse.

In female rats, a daily dose of 0.003 mg/kg for 2 weeks prior to mating and throughout the mating period inhibited conception. This dose represents approximately 1/28 the maximum recommended human dose calculated on a body surface area basis using total mg/m^2/week in rats and mg/m^2/week for a 50 kg human.

Pregnancy: Teratogenic Effects: Category B.

Reproduction studies have been performed with cabergoline in mice, rats, and rabbits administered by gavage.

(Multiples of the maximum recommended human dose in this section are calculated on a body surface area basis using total mg/m^2/week for animals and mg/m^2/week for a 50 kg human.)

There were maternotoxic effects but no teratogenic effects in mice given cabergoline at doses up to 8 mg/kg/day (approximately 55 times the maximum recommended human dose) during the period of organogenesis.

A dose of 0.012 mg/kg/day (approximately 1/7 the maximum recommended human dose) during the period of organogenesis in rats caused an increase in post-implantation embryofetal losses. These losses could be due to the prolactin inhibitory properties of cabergoline in rats. At daily doses of 0.5 mg/kg/day (approximately 19 times the maximum recommended human dose) during the period of organogenesis in the rabbit, cabergoline caused maternotoxicity characterized by a loss of body weight and decreased food consumption. Doses of 4 mg/kg/day (approximately 150 times the maximum recommended human dose) during the period of organogenesis in the rabbit caused an increased occurrence of various malformations. However, in another study in rabbits, no treatment-related malformations or embryofetotoxicity were observed at doses up to 8 mg/kg/day (approximately 300 times the maximum human dose).

In rats, doses higher than 0.003 mg/kg/day (approximately 1/28 the maximum recommended human dose) from 6 days before parturition and throughout the lactation period inhibited growth and caused death of offspring due to decreased milk secretion.

There are, however, no adequate and well-controlled studies in pregnant women. Because animal reproduction studies are not always predictive of human response, this drug should be used during pregnancy only if clearly needed.

Nursing Mothers:

It is not known whether this drug is excreted in human milk. Because many drugs are excreted in human milk and because of the potential for serious adverse reactions in nursing infants from cabergoline, a decision should be made whether to discontinue nursing or to discontinue the drug, taking into account the importance of the drug to the mother. Use of cabergoline for the inhibition or suppression of physiologic lactation is not recommended (see PRECAUTIONS section).

The prolactin-lowering action of cabergoline suggests that it will interfere with lactation. Due to this interference with lactation, cabergoline should not be given to women postpartum who are breastfeeding or who are planning to breastfeed.

Pediatric Use:

Safety and effectiveness of cabergoline in pediatric patients have not been established.

Geriatric Use:

Clinical studies of cabergoline did not include sufficient numbers of subjects aged 65 and over to determine whether they respond differently from younger patients. Other reported clinical experience has not identified differences in responses between the elderly and younger patients. In general, dose selection for an elderly patient should be cautious, usually starting at the low end of the dosing range, reflecting the greater frequency of decreased hepatic, renal, or cardiac function, and of concomitant disease or other drug therapy.

ADVERSE REACTIONS

The safety of Cabergoline Tablets has been evaluated in more than 900 patients with hyperprolactinemic disorders. Most adverse events were mild or moderate in severity.

In a 4-week, double-blind, placebo-controlled study, treatment consisted of placebo or cabergoline at fixed doses of 0.125, 0.5, 0.75, or 1 mg twice weekly. Doses were halved during the first week. Since a possible dose-related effect was observed for nausea only, the four cabergoline treatment groups have been combined. The incidence of the most common adverse events during the placebo-controlled study is presented in the following table.

Incidence of Reported Adverse Events During the 4-Week, Double-Blind, Placebo-Controlled Trial
Adverse Event [Reported at ≥1% for cabergoline] | Cabergoline (n=168) 0.125 to 1 mg two times a week | Placebo (n=20)
 | Number (percent)
Gastrointestinal
Nausea | 45 (27) | 4 (20)
Constipation | 16 (10) | 0
Abdominal pain | 9 (5) | 1 (5)
Dyspepsia | 4 (2) | 0
Vomiting | 4 (2) | 0
Central and Peripheral Nervous System
Headache | 43 (26) | 5 (25)
Dizziness | 25 (15) | 1 (5)
Paresthesia | 2 (1) | 0
Vertigo | 2 (1) | 0
Body As a Whole
Asthenia | 15 (9) | 2 (10)
Fatigue | 12 (7) | 0
Hot flashes | 2 (1) | 1 (5)
Psychiatric
Somnolence | 9 (5) | 1 (5)
Depression | 5 (3) | 1 (5)
Nervousness | 4 (2) | 0
Autonomic Nervous System
Postural hypotension | 6 (4) | 0
Reproductive – Female
Breast pain | 2 (1) | 0
Dysmenorrhea | 2 (1) | 0
Vision
Abnormal vision | 2 (1) | 0

In the 8-week, double-blind period of the comparative trial with bromocriptine, cabergoline (at a dose of 0.5 mg twice weekly) was discontinued because of an adverse event in 4 of 221 patients (2%) while bromocriptine (at a dose of 2.5 mg two times a day) was discontinued in 14 of 231 patients (6%). The most common reasons for discontinuation from cabergoline were headache, nausea and vomiting (3, 2, and 2 patients, respectively); the most common reasons for discontinuation from bromocriptine were nausea, vomiting, headache, and dizziness or vertigo (10, 3, 3, and 3 patients, respectively). The incidence of the most common adverse events during the double-blind portion of the comparative trial with bromocriptine is presented in the following table.

Incidence of Reported Adverse Events During the 8-Week, Double-Blind Period of the Comparative Trial With Bromocriptine
Adverse Event [Reported at ≥1% for cabergoline] | Cabergoline (n=221) | Bromocriptine (n=231)
 | Number (percent)
Gastrointestinal
Nausea | 63 (29) | 100 (43)
Constipation | 15 (7) | 21 (9)
Abdominal pain | 12 (5) | 19 (8)
Dyspepsia | 11 (5) | 16 (7)
Vomiting | 9 (4) | 16 (7)
Dry mouth | 5 (2) | 2 (1)
Diarrhea | 4 (2) | 7 (3)
Flatulence | 4 (2) | 3 (1)
Throat irritation | 2 (1) | 0
Toothache | 2 (1) | 0
Central and Peripheral Nervous System
Headache | 58 (26) | 62 (27)
Dizziness | 38 (17) | 42 (18)
Vertigo | 9 (4) | 10 (4)
Paresthesia | 5 (2) | 6 (3)
Body As a Whole
Asthenia | 13 (6) | 15 (6)
Fatigue | 10 (5) | 18 (8)
Syncope | 3 (1) | 3 (1)
Influenza-like symptoms | 2 (1) | 0
Malaise | 2 (1) | 0
Periorbital edema | 2 (1) | 2 (1)
Peripheral edema | 2 (1) | 1
Psychiatric
Depression | 7 (3) | 5 (2)
Somnolence | 5 (2) | 5 (2)
Anorexia | 3 (1) | 3 (1)
Anxiety | 3 (1) | 3 (1)
Insomnia | 3 (1) | 2 (1)
Impaired concentration | 2 (1) | 1
Nervousness | 2 (1) | 5 (2)
Cardiovascular
Hot flashes | 6 (3) | 3 (1)
Hypotension | 3 (1) | 4 (2)
Dependent edema | 2 (1) | 1
Palpitation | 2 (1) | 5 (2)
Reproductive – Female
Breast pain | 5 (2) | 8 (3)
Dysmenorrhea | 2 (1) | 1
Skin and Appendages
Acne | 3 (1) | 0
Pruritus | 2 (1) | 1
Musculoskeletal
Pain | 4 (2) | 6 (3)
Arthralgia | 2 (1) | 0
Respiratory
Rhinitis | 2 (1) | 9 (4)
Vision
Abnormal vision | 2 (1) | 2 (1)

Other adverse events that were reported at an incidence of <1.0% in the overall clinical studies follow.

Body As a Whole: facial edema, influenza-like symptoms, malaise
Cardiovascular System: hypotension, syncope, palpitations
Digestive System: dry mouth, flatulence, diarrhea, anorexia
Metabolic and Nutritional System: weight loss, weight gain
Nervous System: somnolence, nervousness, paresthesia, insomnia, anxiety
Respiratory System: nasal stuffiness, epistaxis
Skin and Appendages: acne, pruritus
Special Senses: abnormal vision
Urogenital System: dysmenorrhea, increased libido

The safety of cabergoline has been evaluated in approximately 1,200 patients with Parkinson’s disease in controlled and uncontrolled studies at dosages of up to 11.5 mg/day which greatly exceeds the maximum recommended dosage of cabergoline for hyperprolactinemic disorders. In addition to the adverse events that occurred in the patients with hyperprolactinemic disorders, the most common adverse events in patients with Parkinson’s disease were dyskinesia, hallucinations, confusion, and peripheral edema. Heart failure, pleural effusion, pulmonary fibrosis, and gastric or duodenal ulcer occurred rarely. One case of constrictive pericarditis has been reported.

Post-marketing Surveillance data

The following events have been reported in association with cabergoline: cardiac valvulopathy and extracardiac fibrotic reactions

Other events have been reported in association with cabergoline: impulse control/compulsive behavior symptoms, including hypersexuality, increased libido and pathological gambling (See PRECAUTIONS, Psychiatric). In addition, cases of alopecia, aggression, and psychotic disorder have been reported in patients taking cabergoline. Some of these reports have been in patients who have had prior adverse reactions to dopamine agonist products.

To report SUSPECTED ADVERSE REACTIONS, contact SOLA Pharmaceuticals at 1-1-866-747-7365 or FDA at 1-800-FDA-1088 or www.fda.gov/medwatch.

OVERDOSAGE

Overdosage might be expected to produce nasal congestion, syncope, or hallucinations. Measures to support blood pressure should be taken if necessary.

DOSAGE AND ADMINISTRATION

The recommended dosage of Cabergoline Tablets, USP for initiation of therapy is 0.25 mg twice a week. Dosage may be increased by 0.25 mg twice weekly up to a dosage of 1 mg twice a week according to the patient’s serum prolactin level. Before initiating treatment, cardiovascular evaluation should be performed and echocardiography should be considered to assess for valvular disease.

Dosage increases should not occur more rapidly than every 4 weeks, so that the physician can assess the patient's response to each dosage level. If the patient does not respond adequately, and no additional benefit is observed with higher doses, the lowest dose that achieved maximal response should be used and other therapeutic approaches considered. Patients receiving long term treatment with Cabergoline should undergo periodic assessment of their cardiac status and echocardiography should be considered.

After a normal serum prolactin level has been maintained for 6 months, cabergoline may be discontinued, with periodic monitoring of the serum prolactin level to determine whether or when treatment with cabergoline should be reinstituted. The durability of efficacy beyond 24 months of therapy with cabergoline has not been established.

HOW SUPPLIED

Cabergoline Tablets, USP are a white to off-white, oval shape, flat face, beveled edge tablet containing 0.5 mg cabergoline USP. Each tablet is debossed “P” bisect line “P” on one side and “673" on the other side.

Cabergoline Tablets, USP are available as follows:

Bottles of 8 tablets | NDC 70512-860-08

STORAGE

Store at controlled room temperature 20° to 25° C (68° to 77° F) [see USP Controlled Room Temperature]. Dispense in original container.

Distributed by:
SOLA Pharmaceuticals
Baton Rouge, LA 70810

PRINCIPAL DISPLAY PANEL

NDC 70512- 860-08
Cabergoline
Tablets, USP
0.5 mg
8 Tablets Rx only
Sola
Pharmaceuticals
Each tablet contains:
Cabergoline, USP ......... 0.5 mg
USUAL DOSAGE:
See accompanying product literature.
KEEP THIS AND ALL DRUGS
OUT OF REACH OF CHILDREN.
Dispense in original container
Store at Controlled Room
Temperature 20° to 25°C
(68° to 77°F) (see USP).
R02/23 LCS-002-01-01
Distributed by:
SOLA Pharmaceuticals, LLC
Baton Rouge, LA 70810